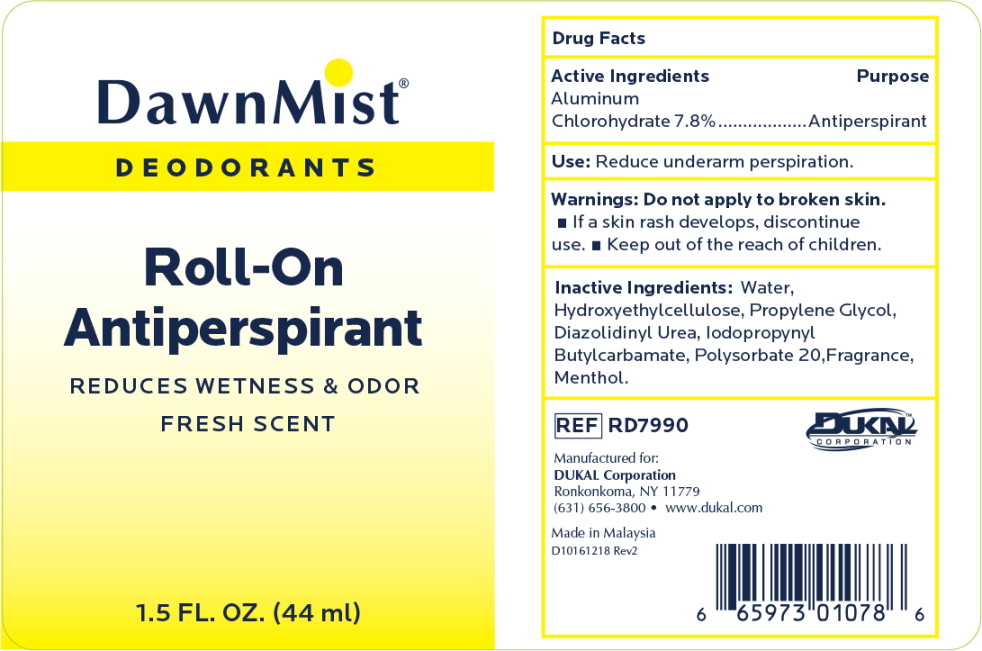 DRUG LABEL: DawnMist Antiperspirant Deodorant
NDC: 65517-1021 | Form: LOTION
Manufacturer: Dukal LLC
Category: otc | Type: HUMAN OTC DRUG LABEL
Date: 20240723

ACTIVE INGREDIENTS: ALUMINUM CHLOROHYDRATE 78 mg/1 mL
INACTIVE INGREDIENTS: HYDROXYETHYL CELLULOSE (4000 CPS AT 1%); WATER; PROPYLENE GLYCOL; DIAZOLIDINYL UREA; IODOPROPYNYL BUTYLCARBAMATE; POLYSORBATE 20; MENTHOL

DawnMist Antiperspirant Deodorant

Active Ingredient

Aluminum Chlorohydrate 7.8%

Purpose

Antiperspirant

Use

- Reduces underarm perspiration.

Warnings

For external use only.

Do not use

on broken skin.

Discontinue use if

■irritation and redness
develop ■ If condition persists for more than 72
hours consult a doctor.

Ask a doctor before use

if you have kidney disease.

Keep out of reach of children

■If swallowed, get medical help and contact Poison Control Center right away ■ Use only as directed

Directions

Apply to underarms only.

Inactive Ingredients

Water, Hydroxyethyl Cellulose, Propylene Glycol, Diazolidinyl Urea, Iodopropynyl Butylcarbamate, Polysorbate 20, Menthol

Principal Display Panel - Bottle Label

DawnMist®

DEODORANTS

Roll-On
Antiperspirant

REDUCES WETNESS & ODOR

FRESH SCENT

1.5 FL. OZ. (44ml)